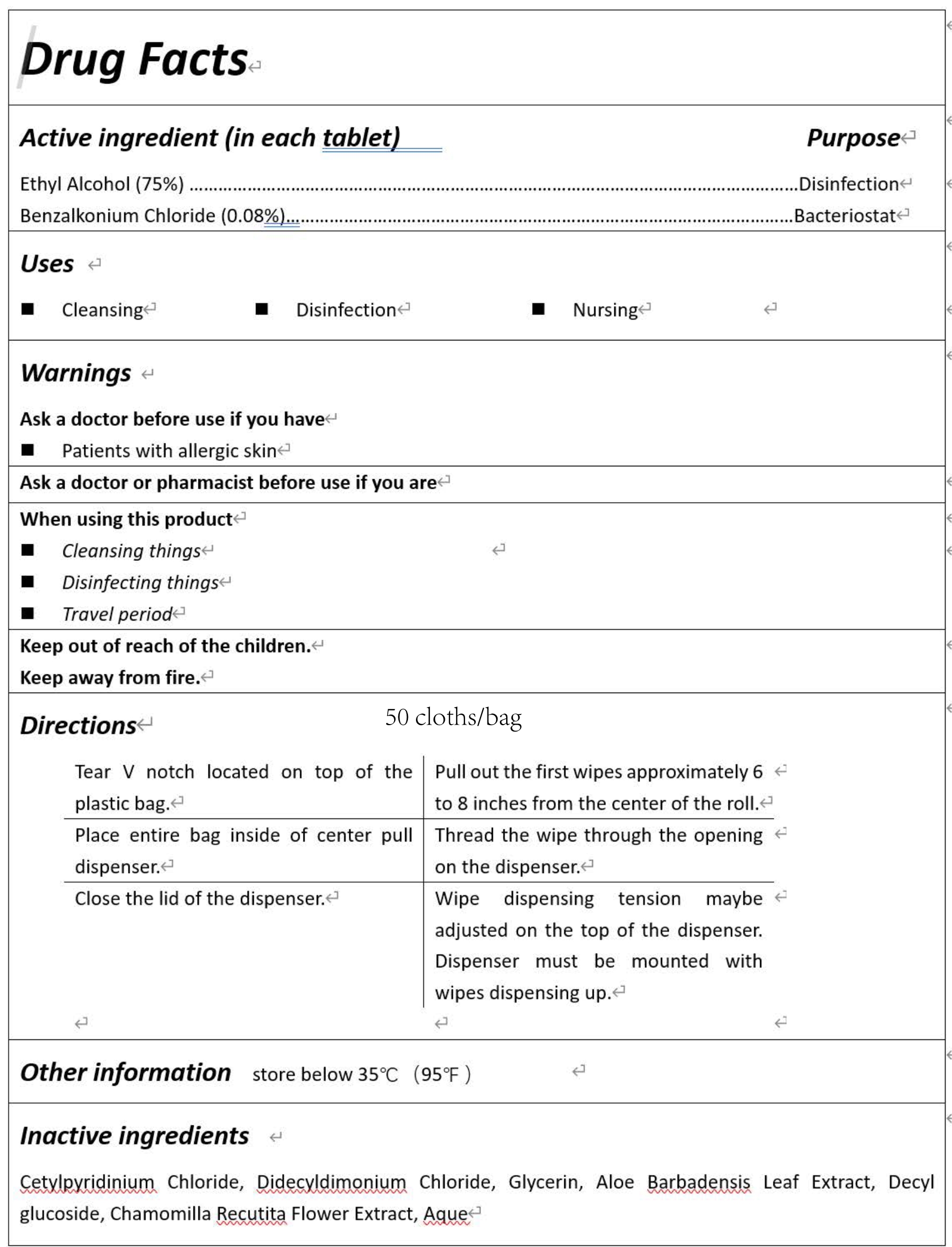 DRUG LABEL: Disinfecting wet wipes
NDC: 81838-001 | Form: PATCH
Manufacturer: Changzhou MeiMuSen New Material Technology Co., Ltd
Category: otc | Type: HUMAN OTC DRUG LABEL
Date: 20210424

ACTIVE INGREDIENTS: ALCOHOL 75 g/100 1; BENZALKONIUM 0.08 g/100 1
INACTIVE INGREDIENTS: GLYCERIN; CETYLPYRIDINIUM CHLORIDE; WATER; ALOE VERA LEAF; DECYL GLUCOSIDE; CHRYSANTHEMUM X MORIFOLIUM WHOLE; DIDECYLDIMONIUM CHLORIDE

81838-001
Disinfecting wet wipes

Active Ingredient(s)

Ethyl Alcohol(75%)
Benzalkonium Chloride(0.08%)

Purpose

Disinfection
Bacteriostat

Use

■Cleansing
■Disinfection
■Nursing

Warnings

Ask a doctor before use if you have
Patients with allergic skin Ask a doctor or pharmacist before use if you are
When using this product
Cleansing things
Disinfecting things
Travel period
Keep out of reach of the children.
Keep away from fire.

Do not use

/

When using this product
Cleansing things
Disinfecting things
Travel period
Keep out of reach of the children.
Keep away from fire.

STOP USE

/

Keep out of reach of the children.

Directions

Tear Vnotch located on top of the plastic bag.
Place entire bag inside of center pull dispenser.
Close the lid of the dispenser.
Pullout the first wipes approximately 6 to 8 inches from the center of the roll.
Thread the wipe through the opening on the dispenser.
Wipedispensingtensionmaybe adjusted on the top of the dispenser.
Dispensermustbemountedwith wipes dispensing up.

Other information

store below 35℃(95℉)

Inactive ingredients

Cetylpyridinium Chloride, Didecyldimonium Chloride,
Glycerin, Aloe Barbadensis Leaf Extract,
Decylglucoside, Chamomilla Recutita Flower Extract, Aque

Package Label - Principal Display Panel

81838-001-01 50CLOTH in 1BAG